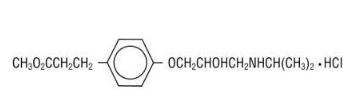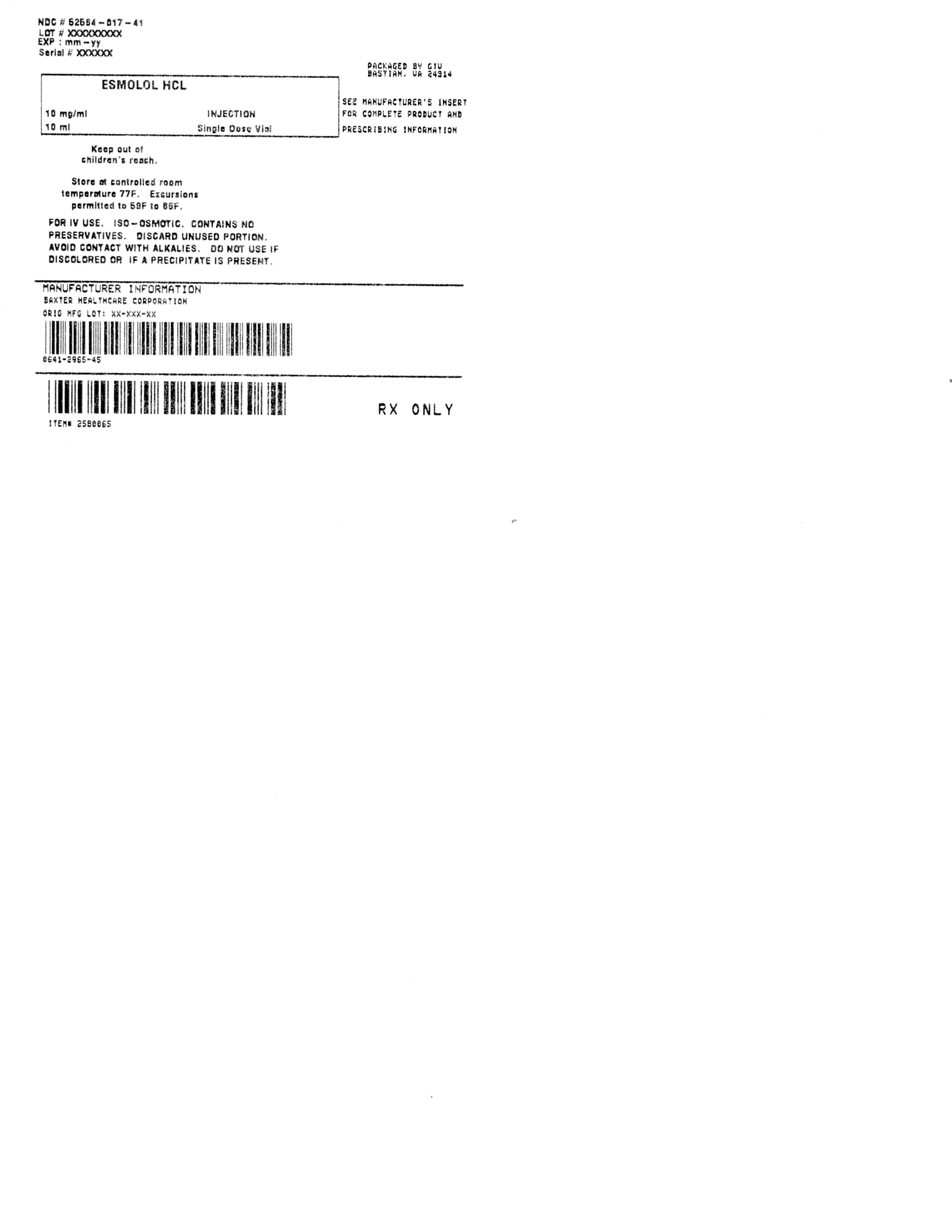 DRUG LABEL: Esmolol
NDC: 52584-017 | Form: INJECTION
Manufacturer: General Injectables & Vaccines, Inc
Category: prescription | Type: HUMAN PRESCRIPTION DRUG LABEL
Date: 20170118

ACTIVE INGREDIENTS: Esmolol Hydrochloride 10 mg/1 mL

Esmolol HCL 10 mg/mL Injection 10mL Single Dose Vial

Description

Ready-to-use Vials
10 mL Vials
Iso-Osmotic Solution of Esmolol Hydrochloride in Sodium Chloride
For Intravenous Use
Can be used for direct intravenous use.
Esmolol Hydrochloride concentration = 10 milligrams/mL (10,000 micrograms/mL)
Single Patient Use Only
No Preservatives Added
Rx only

DESCRIPTION
Esmolol hydrochloride is a beta1-selective (cardioselective) adrenergic receptor blocking agent with a very short duration of action (elimination half-life is approximately 9 minutes). Esmolol Hydrochloride is:
(±)-Methyl p- [2-hydroxy-3- (isopropylamino) propoxy] hydrocinnamate hydrochloride and has the following structure:

Esmolol hydrochloride has the empirical formula C16H26NO4Cl and a molecular weight of 331.8. It has one asymmetric center and exists as an enantiomeric pair. Esmolol hydrochloride is a white to off-white crystalline powder. It is a relatively hydrophilic compound which is very soluble in water and freely soluble in alcohol. Its partition coefficient (octanol/water) at pH 7.0 is 0.42 compared to 17.0 for propranolol. Esmolol Hydrochloride Injection Esmolol Hydrochloride Injection is a clear, colorless to light yellow, sterile, nonpyrogenic, iso-osmotic solution of esmolol

hydrochloride in sodium chloride. 100 mg, 10 mL Single Dose Vial– Each mL contains 10 mg Esmolol Hydrochloride, 5.9 mg Sodium Chloride, USP and Water for Injection, USP; buffered with 2.8 mg Sodium Acetate Trihydrate, USP and 0.546 mg Glacial Acetic Acid, USP. Sodium Hydroxide and/or Hydrochloric Acid added, as necessary to adjust pH to 5.0 (4.5-5.5).

Clinical Pharmacology

Esmolol hydrochloride is a beta1-selective (cardioselective) adrenergic receptor blocking agent with rapid onset, a very short duration of action, and no significant intrinsic sympathomimetic or membrane stabilizing activity at therapeutic dosages. Its elimination halflife after intravenous infusion is approximately 9 minutes. Esmolol hydrochloride inhibits the beta1 receptors located chiefly in cardiac muscle, but this preferential effect is not absolute and at higher doses it begins to inhibit beta2 receptors located chiefly in the bronchial and vascular musculature.

Pharmacokinetics and Metabolism
Esmolol hydrochloride is rapidly metabolized by hydrolysis of the ester linkage, chiefly by the esterases in the cytosol of red blood cells and not by plasma cholinesterases or red cell membrane acetylcholinesterase. Total body clearance in man was found to be about 20 L/kg/hr, which is greater than cardiac output; thus the metabolism of esmolol hydrochloride is not limited by the rate of blood flow to metabolizing tissues such as the liver or affected by hepatic or renal blood flow. Esmolol hydrochloride has a rapid distribution half-life of about 2 minutes and an elimination half-life of about 9 minutes. Using an appropriate loading dose, steady-state blood levels of esmolol hydrochloride for dosages from 50-300 mcg/kg/min (0.05-0.3
mg/kg/min) are obtained within five minutes. (Steady-state is reached in about 30 minutes without the loading dose.) Steady-state blood levels of esmolol hydrochloride increase linearly over this dosage range and elimination kinetics are dose-independent over this range. Steady-state blood levels are maintained during infusion but decrease rapidly after termination of the infusion. Because of its short half-life, blood levels of esmolol hydrochloride can be rapidly altered by increasing or decreasing the infusion rate and rapidly eliminated by discontinuing the infusion.
Consistent with the high rate of blood-based metabolism of esmolol hydrochloride, less than 2% of the drug is excreted unchanged in the urine. Within 24 hours of the end of infusion, approximately 73-88% of the dosage has been accounted for in the urine as the acid metabolite of esmolol hydrochloride. Metabolism of esmolol hydrochloride results in the formation of the corresponding free acid and methanol. The acid metabolite has been shown in animals to have about 1/1500th the activity of esmolol and in normal volunteers its blood levels do not correspond to the level of beta blockade. The acid metabolite has an elimination half-life of about 3.7 hours and is excreted in the urine with a patients with renal disease, with the elimination half-life increased to about ten-fold that of normals, and plasma levels considerably elevated. Methanol blood levels, monitored in subjects receiving esmolol hydrochloride for up to 6 hours at 300 mcg/kg/min (0.3 mg/kg/ min) and 24 hours at 150 mcg/kg/min (0.15 mg/kg/min), approximated endogenous levels and were less than 2% of levels usually associated with methanol toxicity. Esmolol hydrocloride has been shown to be 55% bound to human plasma protein, while the acid metabolite is only 10% bound.

Pharmacodynamics
Clinical pharmacology studies in normal volunteers have confirmed the beta blocking activity of esmolol hydrochloride, showing reduction in heart rate at rest and during exercise, and attenuation of isoproterenol-induced increases in heart rate. Blood levels of esmolol hydrochloride have been shown to correlate with extent of beta blockade. After termination of infusion, substantial recovery from beta blockade is observed in 10-20 minutes. In human electrophysiology studies, esmolol hydrochloride produced effects typical of a beta blocker; a decrease in the heart rate, increase in sinus cycle length, prolongation of the sinus node recovery time, prolongation of the AH interval during normal sinus rhythm and during atrial pacing, and an increase in antegrade Wenckebach cycle length. In patients undergoing radionuclide angiography, esmolol hydrochloride, at dosages of 200 mcg/kg/min (0.2 mg/kg/min), produced reductions in heart rate, systolic blood pressure, rate pressure product, left and right ventricular ejection fraction and cardiac index at rest, which were similar in magnitude to those produced by intravenous propranolol (4 mg). During exercise, esmolol hydrochloride produced reductions in heart rate, rate pressure product and cardiac index which were also similar to those produced by propranolol,
but produced a significantly larger fall in systolic blood pressure. In patients undergoing cardiac catheterization, the maximum therapeutic dose of 300 mcg/kg/min (0.3 mg/kg/min) of esmolol hydrochloride produced similar effects and, in addition, there were small, clinically insignificant increases in the left ventricular end diastolic pressure and pulmonary capillary wedge pressure. At thirty minutes after the discontinuation of esmolol hydrochloride infusion, all of the hemodynamic parameters had returned to pretreatment levels. The relative cardioselectivity of esmolol hydrochloride was demonstrated in 10 mildly asthmatic patients. Infusions of esmolol hydrochloride [100, 200 and 300 mcg/kg/min (0.1, 0.2 and 0.3 mg/kg/min)] produced no significant increases in specific airway resistance compared to placebo. At 300 mcg/kg/min (0.3 mg/kg/min), esmolol hydrochloride produced slightly enhanced bronchomotor sensitivity to dry air stimulus. These effects were not clinically significant, and esmolol hydrochloride was well tolerated by all patients. Six of the patients also received intravenous propranolol, and at a dosage of 1 mg, two experienced significant, symptomatic bronchospasm requiring bronchodilator treatment. One other propranolol-treated patient also experienced dry air-induced bronchospasm. No adverse pulmonary effects were observed in patients with COPD who received therapeutic dosages of esmolol hydrochloride for treatment of supraventricular tachycardia (51 patients) or in perioperative settings (32 patients).

Supraventricular Tachycardia
In two multicenter, randomized, double-blind, controlled comparisons of esmolol hydrochloride with placebo and propranolol, maintenance doses of 50 to 300 mcg/kg/min (0.05 to 0.3 mg/kg/min) of esmolol hydrochloride were found to be more effective than placebo and about as effective as propranolol, 3-6 mg given by bolus injections, in the treatment of supraventricular tachycardia, principally atrial fibrillation and atrial flutter. The majority of these patients developed their arrhythmias postoperatively. About 60-70% of the patients treated with esmolol hydrochloride had a desired therapeutic effect (either a 20% reduction in heart rate, a decrease in heart rate to less than 100 bpm, or, rarely, conversion to NSR) and about 95% of those who responded did so at a dosage of 200 mcg/kg/min (0.2 mg/kg/min) or less. The average effective dosage of esmolol hydrochloride was approximately 100-115 mcg/ kg/min (0.1-0.115 mg/kg/min) in the two studies. Other multicenter baseline-controlled studies gave essentially similar results. In the comparison with propranolol, about 50% of patients in both the esmolol hydrochloride and propranolol groups were on concomitant digoxin. Response rates were slightly higher with both beta blockers in the digoxin-treated patients. In all studies significant decreases of blood pressure occurred in 20-50% of patients, identified either as adverse reaction reports by investigators, or by observation of systolic pressure less than 90 mmHg or diastolic pressure less than 50 mmHg. The hypotension was symptomatic (mainly diaphoresis or dizziness) in about 12% of patients, and therapy was discontinued in about 11% of patients,
about half of whom were symptomatic. In comparison to propranolol, hypotension was about three times as frequent with esmolol hydrochloride, 53% vs. 17%. The hypotension was rapidly reversible with decreased infusion rate or after discontinuation of therapy with esmolol hydrochloride. For both esmolol hydrochloride and propranolol, hypotension was reported less frequently in patients receiving concomitant digoxin.

Indication and Usage

Supraventricular Tachycardia
Esmolol hydrochloride is indicated for the rapid control of ventricular rate in patients with atrial fibrillation or atrial flutter in perioperative, postoperative, or other emergent circumstances where short term control of ventricular rate with a short-acting agent is desirable. Esmolol hydrochloride is also indicated in noncompensatory sinus tachycardia where, in the physician’s judgment, the rapid heart rate requires specific intervention. Esmolol hydrochloride is not intended for use in chronic settings where transfer to another agent is anticipated.

Intraoperative and Postoperative Tachycardia and/or Hypertension
Esmolol hydrochloride is indicated for the treatment of tachycardia and hypertension that occur during induction and tracheal intubation, during surgery, on emergence from anesthesia, and in the postoperative period, when in the physician’s judgment such specific intervention is considered indicated. Use of esmolol hydrochloride to prevent such events is not recommended.

Contraindications

Esmolol hydrochloride is contraindicated in patients with sinus bradycardia, heart block greater than first degree, cardiogenic shock or overt heart failure (see WARNINGS).

Warnings

Hypotension
In clinical trials 20-50% of patients treated with esmolol hydrochloride have experienced hypotension, generally defined as systolic pressure less than 90 mmHg and/or diastolic pressure less than 50 mmHg. About 12% of the patients have been symptomatic (mainly diaphoresis or dizziness). Hypotension can occur at any dose but is dose-related so that doses beyond 200 mcg/kg/min (0.2 mg/kg/ min) are not recommended. Patients should be closely monitored, especially if pretreatment blood pressure is low. Decrease of dose or termination of infusion reverses hypotension, usually within 30 minutes.

Cardiac Failure
Sympathetic stimulation is necessary in supporting circulatory function in congestive heart failure, and beta blockade carries the potential hazard of further depressing myocardial contractility and precipitating more severe failure. Continued depression of the myocardium with beta blocking agents over a period of time can, in some cases, lead to cardiac failure. At the first sign or symptom of impending cardiac failure, esmolol hydrochloride should be withdrawn. Although withdrawal may be sufficient because of the short elimination half-life of esmolol hydrochloride, specific treatment may also be considered (seeOVERDOSAGE). The use of esmolol hydrochloride for control of ventricular response in patients with supraventricular arrhythmias should be undertaken with caution when the patient is compromised hemodynamically or is taking other drugs that decrease any or all of the following: peripheral resistance, myocardial filling, myocardial contractility, or electrical impulse propagation in the myocardium. Despite the rapid onset and offset of the effects of esmolol hydrochloride, several cases of death have been reported in complex clinical states where esmolol hydrochloride was presumably being used to control ventricular rate.

Intraoperative and Postoperative Tachycardia and/or Hypertension
Esmolol hydrochloride should not be used as the treatment for hypertension in patients in whom the increased blood pressure is primarily due to the vasoconstriction associated with hypothermia.
Bronchospastic Diseases
PATIENTS WITH BRONCHOSPASTIC DISEASES SHOULD, IN GENERAL, NOT RECEIVE BETA BLOCKERS. Because of its relative beta1 selectivity and titratability, esmolol hydrochloride may be used with caution in patients with bronchospastic diseases. However, since beta1 selectivity is not absolute, esmolol hydrochloride should be carefully titrated to obtain the lowest
possible effective dose. In the event of bronchospasm, the infusion should be terminated immediately; a beta2 stimulating agent may be administered if conditions warrant but should be used with particular caution as patients already have rapid ventricular rates.

Diabetes Mellitus and Hypoglycemia
Esmolol hydrochloride should be used with caution in diabetic patients requiring a beta blocking agent. Beta blockers may mask tachycardia occurring with hypoglycemia, but other manifestations such as dizziness and sweating may not be significantly affected.

Precautions

General
Infusion concentrations of 20 mg/mL were associated with more serious venous irritation, including thrombophlebitis, than concentrations of 10 mg/mL. Extravasation of 20 mg/mL may lead to a serious local reaction and possible skin necrosis. Concentrations greater than 10 mg/mL or infusion into small veins or through a butterfly catheter should be avoided. Because the acid metabolite of esmolol hydrochloride is primarily excreted unchanged by the kidney, esmolol hydrochloride should be administered with caution to patients with impaired renal function. The elimination half-life of the acid metabolite was prolonged tenfold and the plasma level was considerably elevated in patients with end-stage renal disease. Care should be taken in the intravenous administration of esmolol hydrochloride as sloughing of the skin and necrosis have been reported in association with infiltration and extravasation of intravenous infusions.
Drug Interactions
Catecholamine-depleting drugs, e.g., reserpine, may have an additive effect when given with beta blocking agents. Patients treated concurrently with esmolol hydrochloride and a catecholamine depletor should therefore be closely observed for evidence of hypotension or marked bradycardia, which may result in vertigo, syncope, or postural hypotension.
A study of interaction between esmolol hydrochloride and warfarin showed that concomitant administration of esmolol hydrochloride and warfarin does not alter warfarin plasma levels. Esmolol hydrochloride concentrations were equivocally higher when given with warfarin, but this is not likely to be clinically important. When digoxin and esmolol hydrochloride were concomitantly administered intravenously to normal volunteers, there was a 10-20% increase in digoxin blood levels at some time points. Digoxin did not affect esmolol hydrochloride pharmacokinetics. When intravenous morphine and esmolol hydrochloride were concomitantly administered in normal subjects, no effect on morphine blood levels was seen, but esmolol hydrochloride steady-state blood levels were increased by 46% in the presence of morphine. No other pharmacokinetic parameters were changed. The effect of esmolol hydrochloride on the duration of succinylcholine-induced neuromuscular blockade was studied in patients undergoing surgery. The onset of neuromuscular blockade by succinylcholine was unaffected by esmolol hydrochloride, but the duration of neuromuscular blockade was prolonged from 5 minutes to 8 minutes. Although the interactions observed in these studies do not appear to be of major clinical importance, esmolol hydrochloride should be titrated with caution in patients being treated concurrently with digoxin, morphine, succinylcholine or warfarin. While taking beta blockers, patients with a history of severe anaphylactic reaction to a variety of allergens may be more reactive to repeated challenge, either accidental, diagnostic, or therapeutic. Such patients may be unresponsive to the usual doses of epinephrine used to treat allergic reaction. Caution should be exercised when considering the use of esmolol hydrochloride and verapamil in patients with depressed myocardial function. Fatal cardiac arrests have occurred in patients receiving both drugs. Additionally, esmolol hydrochloride should not be used to control supraventricular tachycardia in the presence of agents which are vasoconstrictive and inotropic such as dopamine, epinephrine, and norepinephrine because of the danger of blocking cardiac contractility when systemic vascular resistance is high.

Carcinogenesis, Mutagenesis, Impairment of Fertility
Because of its short term usage no carcinogenicity, mutagenicity or reproductive performance studies have been conducted with esmolol hydrochloride.

Pregnancy Category C
Teratogenicity studies in rats at intravenous dosages of esmolol hydrochloride up to 3000 mcg/kg/min (3 mg/kg/min) (ten times the maximum human maintenance dosage) for 30 minutes daily produced no evidence of maternal toxicity, embryotoxicity or teratogenicity, while a dosage of 10,000 mcg/kg/min (10 mg/kg/min) produced maternal toxicity and lethality. In rabbits, intravenous dosages up to 1000 mcg/kg/min (1 mg/kg/min) for 30 minutes daily produced no evidence of maternal toxicity, embryotoxicity or teratogenicity, while 2500 mcg/kg/min (2.5 mg/kg/min) produced minimal maternal toxicity and increased fetal resorptions. Although there are no adequate and well-controlled studies in pregnant women, use of esmolol in the last trimester of pregnancy or during labor or delivery has been reported to cause fetal bradycardia, which continued after termination of drug infusion. Esmolol hydrochloride should be used during pregnancy only if the potential benefit justifies the potential risk to the fetus.

Nursing Mothers
It is not known whether esmolol hydrochloride is excreted in human milk; however, caution should be exercised when esmolol hydrochloride is administered to a nursing woman.

Pediatric Use
The safety and effectiveness of esmolol hydrochloride in pediatric patients have not been established.

Adverse Reactions

The following adverse reaction rates are based on use of esmolol hydrochloride in clinical trials involving 369 patients with supraventricular tachycardia and over 600 intraoperative and postoperative patients enrolled in clinical trials. Most adverse effects observed in controlled clinical trial settings have been mild and transient. The most important adverse effect has been hypotension (see WARNINGS). Deaths have been reported in post-marketing experience occurring during complex clinical states where esmolol hydrochloride was presumably being used simply to control ventricular rate (see WARNINGS, Cardiac Failure).

Cardiovascular
Symptomatic hypotension (diaphoresis, dizziness) occurred in 12% of patients, and therapy was discontinued in about 11%, about half of whom were symptomatic. Asymptomatic hypotension occurred in about 25% of patients. Hypotension resolved during esmolol hydrochloride infusion in 63% of these patients and within 30 minutes after discontinuation of infusion in 80% of the remaining patients. Diaphoresis accompanied hypotension in 10% of patients. Peripheral ischemia occurred in approximately 1% of patients. Pallor, flushing, bradycardia (heart rate less than 50 beats per minute), chest pain, syncope, pulmonary edema and heart block have each been reported in less than 1% of patients. In two patients without supraventricular tachycardia but with serious coronary artery disease (post inferior myocardial infarction or unstable angina), severe bradycardia/sinus pause/asystole has developed, reversible in both cases with discontinuation of treatment.

Central Nervous System
Dizziness has occurred in 3% of patients; somnolence in 3%; confusion, headache, and agitation in about 2%; and fatigue in about 1% of patients. Paresthesia, asthenia, depression, abnormal thinking, anxiety, anorexia, and lightheadedness were reported in less than 1% of patients. Seizures were also reported in less than 1% of patients, with one death.

Respiratory
Bronchospasm, wheezing, dyspnea, nasal congestion, rhonchi, and rales have each been reported in less than 1% of patients.

Gastrointestinal
Nausea was reported in 7% of patients. Vomiting has occurred in about 1% of patients. Dyspepsia, constipation, dry mouth, and abdominal discomfort have each occurred in less than 1% of patients. Taste perversion has also been reported.

Skin (Infusion Site)
Infusion site reactions including inflammation and induration were reported in about 8% of patients. Edema, erythema, skin discoloration, burning at the infusion site, thrombophlebitis, and local skin necrosis from extravasation have each occurred in less than
1% of patients.

Miscellaneous
Each of the following has been reported in less than 1% of patients: Urinary retention, speech disorder, abnormal vision, midscapular pain, rigors, and fever.

Overdosage

Acute Toxicity
Overdoses of esmolol hydrochloride can cause cardiac arrest. In addition, overdoses can produce bradycardia, hypotension, electromechanical dissociation and loss of consciousness. Cases of massive accidental overdoses of esmolol hydrochloride have occurred due to dilution errors. Some of these overdoses have been fatal while others resulted in permanent disability. Bolus doses in the range of 625 mg to 2.5 g (12.5-50 mg/kg) have been fatal. Patients have recovered completely from overdoses as high as 1.75 g given over one minute or doses of 7.5 g given over one hour for cardiovascular surgery. The patients who survived appear to be those whose circulation could be supported until the effects of esmolol hydrochloride resolved. Because of its approximately 9-minute elimination half-life, the first step in the management of toxicity should be to discontinue the esmolol hydrochloride infusion. Then, based on the observed clinical effects, the following general measures should also be considered.
Bradycardia: Intravenous administration of atropine or another anticholinergic drug.
Bronchospasm: Intravenous administration of a beta2 stimulating agent and/or a theophylline derivative.
Cardiac Failure: Intravenous administration of a diuretic and/or digitalis glycoside. In shock resulting from inadequate cardiac contractility, intravenous administration of dopamine, dobutamine, isoproterenol, or amrinone may be considered.
Symptomatic Hypotension: Intravenous administration of fluids and/or pressor agents.

Dosage and Administration

Dosing Information:

SUPRAVENTRICULAR TACHYCARDIADosage needs to be titrated, using ventricular rate as the guide.
An initial loading dose of 0.5 milligrams/kg (500 micrograms/kg) infused over a minute duration followed by a maintenance infusion of 0.05 milligrams/kg/min (50 micrograms/kg/min) for the next 4 minutes is recommended. This should give a rough guide with respect to the responsiveness of ventricular rate. After the 4 minutes of initial maintenance infusion (total treatment duration being 5 minutes), depending upon the desired ventricular response, the maintenance infusion may be continued at 0.05 mg/kg/min or increased step-wise (e.g. 0.1 mg/kg/min, 0.15 mg/kg/min to a maximum of 0.2 mg/kg/min) with each step being maintained for 4 or more minutes. If more rapid slowing of ventricular response is imperative, the 0.5 mg/kg loading dose infused over a 1 minute period may be repeated, followed by a maintenance infusion of 0.1 mg/kg/min for 4 minutes. Then, depending upon ventricular rate, another (and final) loading dose of 0.5 mg/kg/min infused over a 1 minute period may be administered followed by a maintenance infusion of 0.15 mg/kg/min. If needed, after 4 minutes of the 0.15 mg/kg/min maintenance infusion, the maintenance infusion may be increased to a maximum of 0.2 mg/kg/min. In the absence of loading doses, constant infusion of a single concentration of esmolol reaches pharmacokinetic and pharmacodynamic steady-state in about 30 minutes. Maintenance infusions (with or without loading doses) may be continued for as long as 24 hours. The following table summarizes the above and assumes that 3 loading doses (the maximum recommended) are infused over 1 minute and incremental maintenance doses are required after each loading dose. There should be no 4th loading dose, but the maintenance dose may be incremented one more time.

Elapsed Time | Loading dose (over 1 minute) |  | Maintenance Dose (over 4 minutes)
(minutes) | Micrograms/kg/min | Milligrams/kg/min | micrograms/kg/min | Milligrams kg/min
0-1 | 500 | 0.5
1-5 |  |  | 50 | 0.05
5-6 | 500 | 0.5
6-10 |  |  | 100 | 0.1
10-11 | 500 | 0.5
11-15 |  |  | 150 | 0.15
15-16
16-20 |  |  | *200 | *0.2
more than 20 |  |  | Maintenance dose titrated to heart rate or other clinical endpoing.

*As the desired heart rate or endpoint is approached, the loading infusion may be omitted and the maintenance infusion titrated to 300 mcg/kg/min (0.3 mg/kg/min) or downward as appropriate. Maintenance dosages above 200 mcg/kg/min (0.2 mg/kg/min) have not been shown to have significantly increased benefits. The interval between titration steps may be increased. In the treatment of supraventricular tachycardia, responses to esmolol hydrochloride usually (over 95%) occur within the range of 50 to 200 micrograms/kg/min (0.05 to 0.2 milligrams/kg/min). The average effective dosage is approximately 100 micrograms/kg/ min (0.1 milligrams/kg/min) although dosages as low as 25 micrograms/kg/min (0.025 milligrams/kg/min) have been adequate in some patients. Dosages as high as 300 micrograms/kg/min (0.3 milligrams/kg/min) have been used, but these provide little added effect and increase the rate of adverse effects, so doses greater than 200 micrograms/kg/min are not recommended. Dosage of esmolol hydrochloride in supraventricular tachycardia must be individualized by titration in which each step consists of a loading dosage followed by a maintenance dosage.
This specific dosage regimen has not been studied intraoperatively and, because of the time required for titration, may not be optimal for intraoperative use.
The safety of dosages above 300 mcg/kg/min (0.3 mg/kg/min) has not been studied.
In the event of an adverse reaction, the dosage of esmolol hydrochloride may be reduced or discontinued. If a local infusion site reaction develops, an alternate infusion site should be used and caution should be taken to prevent extravasation. The use of butterfly needles should be avoided.
Abrupt cessation of esmolol hydrochloride in patients has not been reported to produce the withdrawal effects which may occur with abrupt withdrawal of beta blockers following chronic use in coronary artery disease (CAD) patients. However, caution should still be used in abruptly discontinuing infusions of esmolol hydrochloride in CAD patients.
After achieving an adequate control of the heart rate and a stable clinical status in patients with supraventricular tachycardia, transition to alternative antiarrhythmic agents such as propranolol, digoxin, or verapamil, may be accomplished.
A recommended guideline for such a transition is given below but the physician should carefully consider the labeling instructions for the alternative agent selected.

Alternative Agent | Dosage
Propranolol hydrochloride | 10-20 mg q 4-6 hrs
Digoxin | 0.125-0.5 mg q 6 hrs (p.o. or i.v.)
Verapamil | 80 mg q 6 hrs

The dosage of esmolol hydrochloride should be reduced as follows:
1. Thirty minutes following the first dose of the alternative agent, reduce the infusion rate of esmolol hydrochloride by one-half (50%).
2. Following the second dose of the alternative agent, monitor the patient’s response and if satisfactory control is maintained for the first hour, discontinue esmolol hydrochloride.
The use of infusions of esmolol hydrochloride up to 24 hours has been well documented; in addition, limited data from 24-48 hrs
(N=48) indicate that esmolol hydrochloride is well tolerated up to 48 hours.
INTRAOPERATIVE AND POSTOPERATIVE TACHYCARDIA AND/OR HYPERTENSION
In the intraoperative and postoperative settings it is not always advisable to slowly titrate the dose of esmolol hydrochloride to a therapeutic effect. Therefore, two dosing options are presented: immediate control dosing and a gradual control when the physician has time to titrate.
1. Immediate Control
For intraoperative treatment of tachycardia and/or hypertension give an 80 mg (approximately 1 mg/kg) bolus dose over 30 seconds followed by a 150 mcg/kg/min infusion, if necessary. Adjust the infusion rate as required up to 300 mcg/kg/min to maintain desired heart rate and/or blood pressure.
2. Gradual Control
For postoperative tachycardia and hypertension, the dosing schedule is the same as that used in supraventricular tachycardia. To initiate treatment, administer a loading dosage infusion of 500 mcg/kg/min of esmolol hydrochloride for one minute followed by a four-minute maintenance infusion of 50 mcg/kg/min. If an adequate therapeutic effect is not observed within five minutes, repeat the same loading dosage and follow with a maintenance infusion increased to 100 mcg/kg/min (see above SUPRAVENTRICULAR TACHYCARDIA).
Notes:
1. Higher dosages (250-300 mcg/kg/min) may be required for adequate control of blood pressure than those required for the treatment of atrial fibrillation, flutter and sinus tachycardia. One third of the postoperative hypertensive patients required these higher doses.
2. Parenteral drug products should be inspected visually for particulate matter and discoloration prior to administration, whenever solution and container permit.
Directions for Use of the 10 mL Ready-to-use Vial (10 milligrams/mL)
This dosage form is prediluted to provide a ready-to-use, iso-osmotic solution of 10 mg/mL esmolol hydrochloride in sodium chloride recommended for esmolol hydrochloride intravenous administration. It may be used to administer the appropriate esmolol hydrochloride loading dosage infusions by hand-held syringe while the maintenance infusion is being prepared.
The 10 mL Ready-to-use Vial esmolol hydrochloride at a concentration of 10 milligrams/mL. When using a 10 milligrams/mL concentration, a loading dose of 0.5 mg/kg infused over 1 minute period of time, for a 70 kg patient is 3.5 mL.
Compatibility with Commonly Used Intravenous Fluids
Esmolol hydrochloride was tested for compatibility with ten commonly used intravenous fluids at a final concentration of 10 mg
Esmolol Hydrochloride per mL. Esmolol hydrochloride was found to be compatible with the following solutions and was stable for at least 24 hours at controlled room temperature or under refrigeration:
• Dextrose (5%) Injection, USP
• Dextrose (5%) in Lactated Ringer’s Injection
• Dextrose (5%) in Ringer’s Injection
• Dextrose (5%) and Sodium Chloride (0.45%) Injection, USP
• Dextrose (5%) and Sodium Chloride (0.9%) Injection, USP
• Lactated Ringer’s Injection, USP
• Potassium Chloride (40 mEq/liter) in Dextrose (5%) Injection, USP
• Sodium Chloride (0.45%) Injection, USP
• Sodium Chloride (0.9%) Injection, USP
Esmolol hydrochloride is NOT compatible with Sodium Bicarbonate (5%) Injection, USP.

How Supplied

Esmolol Hydrochloride Injection
NDC 0641-2965-45, 100 mg - 10 mL Ready-to-use Vials, Package of 25
Store at 20#-25#C (68#-77#F). Excursions permitted to 15#-30#C (59#-86#F). [See USP Controlled Room Temperature.]
PROTECT FROM FREEZING. Avoid excessive heat.
Baxter is a registered trademark of Baxter International Inc.
Manufactured by
Baxter Healthcare Corporation
Deerfield, IL 60015 USA
For Product Inquiry 1 800 ANA DRUG (1-800-262-3784)
Rev: April 2005